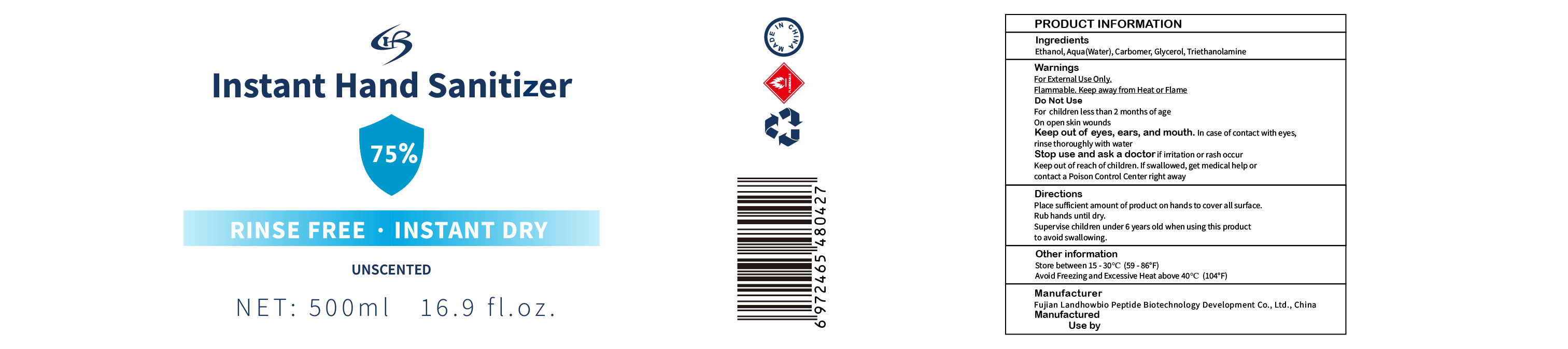 DRUG LABEL: Instant Hand Sanitizer
NDC: 41652-001 | Form: GEL
Manufacturer: FUJIAN LANDHOWBIO PEPTIDE BIOTECHNOLOGY DEVELOPMENT CO. , LTD.
Category: otc | Type: HUMAN OTC DRUG LABEL
Date: 20200810

ACTIVE INGREDIENTS: ALCOHOL 395 g/500 mL
INACTIVE INGREDIENTS: TROLAMINE; WATER; CARBOMER HOMOPOLYMER, UNSPECIFIED TYPE; GLYCERIN

DOSAGE AND ADMINISTRATION

Store between 15 - 30°C (59 - 86°F)
Avoid Freezing and Excessive Heat above 40°C (104°F)

INACTIVE INGREDIENT

Carbomer,Glycerol,Triethanolamine,Aqua

INDICATIONS AND USAGE

Place sufficient amount of product on hands to cover all surface.Rub hands until dry.

ACTIVE INGREDIENT

Ethanol

keep out of reach of children

PURPOSE

Disinfection
Sterilization
No Rinseing

WARNINGS

For External Use Only.Flammable. Keep away from Heat or Flame